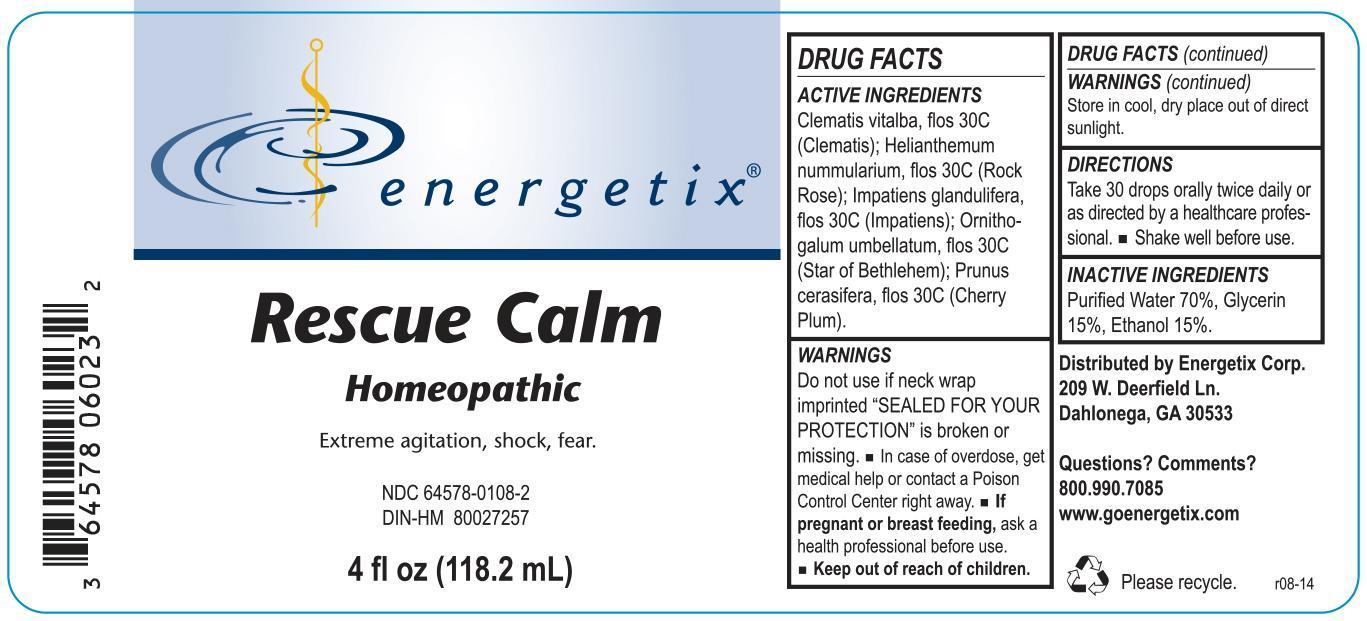 DRUG LABEL: Rescue Calm
NDC: 64578-0108 | Form: LIQUID
Manufacturer: Energetix Corp
Category: homeopathic | Type: HUMAN OTC DRUG LABEL
Date: 20140825

ACTIVE INGREDIENTS: CLEMATIS VITALBA FLOWER 30 [hp_C]/118.2 mL; HELIANTHEMUM NUMMULARIUM FLOWER 30 [hp_C]/118.2 mL; IMPATIENS GLANDULIFERA FLOWER 30 [hp_C]/118.2 mL; ORNITHOGALUM UMBELLATUM FLOWERING TOP 30 [hp_C]/118.2 mL; PRUNUS CERASIFERA FLOWER 30 [hp_C]/118.2 mL
INACTIVE INGREDIENTS: WATER 82.731 mL/118.2 mL; GLYCERIN 17.728 mL/118.2 mL; ALCOHOL 17.728 mL/118.2 mL

Rescue Calm

ACTIVE INGREDIENT

Clematis vitalba, flos 30C (Clematis); Helianthemum nummularium, flos 30C (Rock Rose); Impatiens glandulifera, flos 30C (Impatiens); Ornithogalum umbellatum, flos 30C (Star of Bethlehem); Prunus cerasifera, flos 30C (Cherry Plum).

Do not use if neck wrap imprinted "SEALED FOR YOUR PROTECTION" is broken or missing.

OVERDOSAGE

In case of overdose, get medical help or contact a Poison Control Center right away.

PREGNANCY OR BREAST FEEDING

If pregnant or breast feeding, ask a health professional before use.

Keep out of reach of children.

STORAGE AND HANDLING

Store in cool, dry place out of direct sunlight.

Questions? Comments?
800.990.7085 www.goenergetix.com

PURPOSE

Extreme agitation, shock, fear.

INACTIVE INGREDIENT

Purified Water 70%, Glycerin 15%, Ethanol 15%.

DOSAGE AND ADMINISTRATION

Take 30 drops orally twice daily or as directed by a healthcare professional. Shake well before use.

INDICATIONS AND USAGE

Extreme agitation, shock, fear.